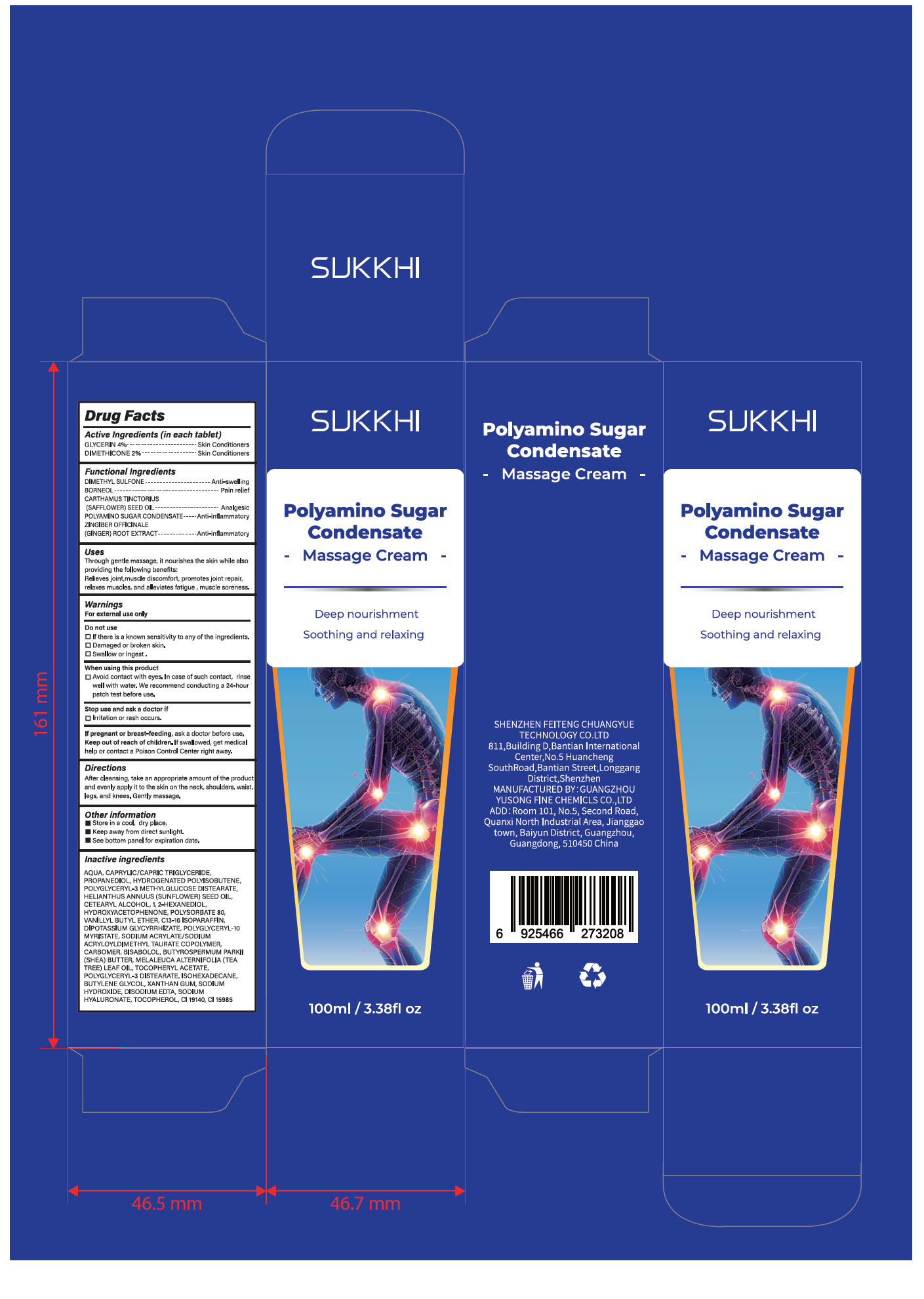 DRUG LABEL: SUKKHI Polyamino Sugar Condensate Massage Cream
NDC: 84558-009 | Form: CREAM
Manufacturer: GUANGZHOU YUSONG FINE CHEMICLS Co., Ltd
Category: otc | Type: HUMAN OTC DRUG LABEL
Date: 20250508

ACTIVE INGREDIENTS: GLYCERIN 4 g/100 mL; DIMETHICONE 2 g/100 mL
INACTIVE INGREDIENTS: VANILLYL BUTYL ETHER; CARTHAMUS TINCTORIUS (SAFFLOWER) SEED OIL; DIMETHYL SULFONE; DIPOTASSIUM GLYCYRRHIZATE; EDETATE DISODIUM; BISABOLOL; AQUA; CAPRYLIC/CAPRIC TRIGLYCERIDE; PROPANEDIOL; HYDROGENATED POLYISOBUTENE (450 MW); POLYGLYCERYL-3 METHYLGLUCOSE DISTEARATE; HELIANTHUS ANNUUS (SUNFLOWER) SEED OIL; CETEARYL ALCOHOL; 1,2-HEXANEDIOL; HYDROXYACETOPHENONE; POLYSORBATE 80; XANTHAN GUM; SODIUM HYDROXIDE; SODIUM ACRYLATE/SODIUM ACRYLOYLDIMETHYLTAURATE COPOLYMER (4000000 MW); TOCOPHEROL; GINGER; POLYGLYCERYL-10 MYRISTATE; CARBOMER; BUTYROSPERMUM PARKII (SHEA) BUTTER; BUTYLENE GLYCOL; CI 15985; BORNEOL; MELALEUCA ALTERNIFOLIA (TEA TREE) LEAF OIL; ISOHEXADECANE; SODIUM HYALURONATE; CI 19140; ALPHA-TOCOPHEROL ACETATE; C13-16 ISOPARAFFIN; POLYGLYCERYL-3 DISTEARATE

84558-009
SUKKHI Polyamino Sugar Condensate Massage Cream

Active Ingredient(s)

GLYCERIN 4%

DIMETHICONE 2%

Purpose

Skin Conditioners

Use

Through gentle massage, it nourishes the skin while also providing the following benefits:
Relieves joint,muscle discomfort, promotes joint repair, relaxes muscles, and alleviates fatigue , muscle soreness.

Warnings

For external use only

Do not use

If there is a known sensitivity to any of the ingredients.
Damaged or broken skin.
Swallow or ingest .

WHEN USING

Avoid contact with eyes. In case of such contact, rinse well with water. We recommend conducting a 24-hour
patch test before use.

STOP USE

Irritation or rash occurs.

KEEP OUT OF REACH OF CHILDREN

If pregnant or breast-feeding, ask a doctor before use. Keep out of reach of children. If swallowed, get medical
help or contact a Poison Control Center right away.

Directions

After cleansing, take an appropriate amount of the product and evenly apply it to the skin on the neck, shoulders, waist,
legs, and knees. Gently massage.

Other information

■Store in a cool, dry place.
■Keep away from direct sunlight.
■See bottom panel for expiration date.

Inactive ingredients

AQUA, CAPRYLIC/CAPRIC TRIGLYCERIDE,PROPANEDIOL, HYDROGENATED POLYISOBUTENE,
POLYGLYCERYL-3 METHYL GLUCOSE DISTEARATE,HELIANTHUS ANNUUS (SUNFL OWER) SEED OIL,
CETEARYL ALCOHOL, 1, 2-HEXANEDIOL, HYDROXYACETOPHENONE, POLYSORBATE 80,
VANILLYL BUTYL ETHER, C13-16 ISOPARAFFIN, DIPOTASSIUM GLYCYRRHIZATE, POLYGLYCERYL-10
MYRISTATE, SODIUM ACRYL .ATE/SODIUM ACRYLOYLDIMETHYL TAURATE COPOLYMER,
CARBOMER, BISABOL OL, BUTYROSPERMUM PARKII (SHEA) BUTTER, MEL _AL .EUCA ALTERNIFOLIA (TEA
TREE) LEAF OIL, TOCOPHERYL ACETATE, POLYGLYCERYL-3 DISTEARATE, ISOHEXADECANE,

BUTYL .ENE GLYCOL, XANTHAN GUM, SODIUM HYDROXIDE, DISODIUM EDTA, SODIUM
HYALURONATE, TOCOPHEROL, CI 19140, CI 15985